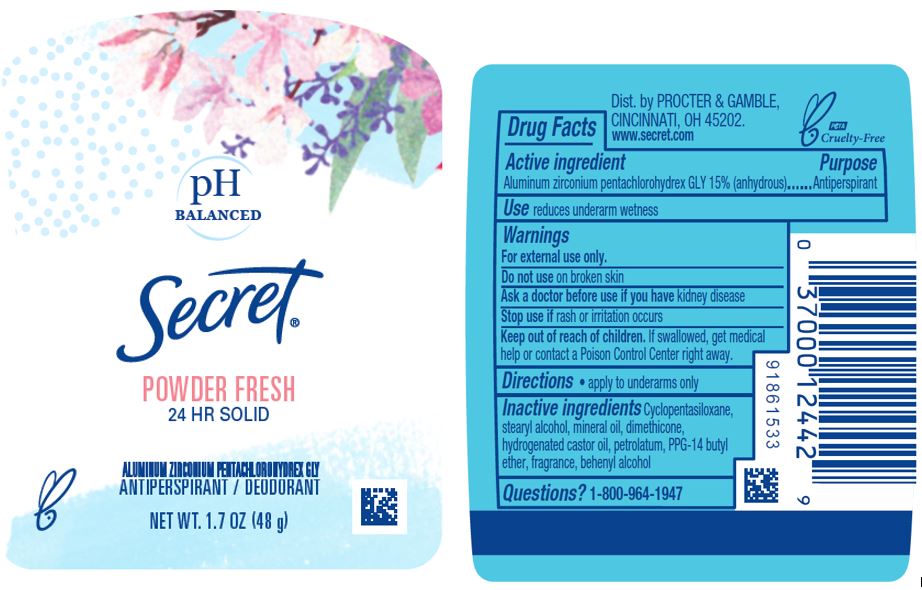 DRUG LABEL: Secret Powder Fresh Antiperspirant and Deodorant
NDC: 69423-624 | Form: STICK
Manufacturer: The Procter & Gamble Manufacturing Company
Category: otc | Type: HUMAN OTC DRUG LABEL
Date: 20251218

ACTIVE INGREDIENTS: ALUMINUM ZIRCONIUM PENTACHLOROHYDREX GLY 15 g/100 g
INACTIVE INGREDIENTS: PETROLATUM; MINERAL OIL; PPG-14 BUTYL ETHER; CYCLOPENTASILOXANE; STEARYL ALCOHOL; DIMETHICONE; HYDROGENATED CASTOR OIL; BEHENYL ALCOHOL

Secret® Wide Solid Powder Fresh Antiperspirant/Deodorant

Drug Facts

Active ingredient

Aluminum zirconium pentachlorohydrex Gly 15% (anhydrous)

Purpose

Antiperspirant

Use

reduces underarm wetness

Warnings

For external use only.

Do not use on broken skin

Ask a doctor before use if you have kidney disease

Stop use if rash or irritation occurs

Keep out of reach of children. If swallowed, get medical help or contact a Poison Control Center right away.

Directions

apply to underarms only

Inactive ingredients

cyclopentasiloxane, stearyl alcohol, mineral oil, dimethicone, hydrogenated castor oil, petrolatum, PPG-14 butyl ether, fragrance, behenyl alcohol

Questions?

1-800-964-1947

Dist. by Procter & Gamble, Cincinnati, OH 45202.

PRINCIPAL DISPLAY PANEL - 48 g Canister Label

pH BALANCED

Secret®

POWDER FRESH

23 HR SOLID

Aluminum zirconium pentachlorohydrex GLY
ANTIPERSPIRANT/DEODORANT

Net Wt. 1.7 OZ (48 g)